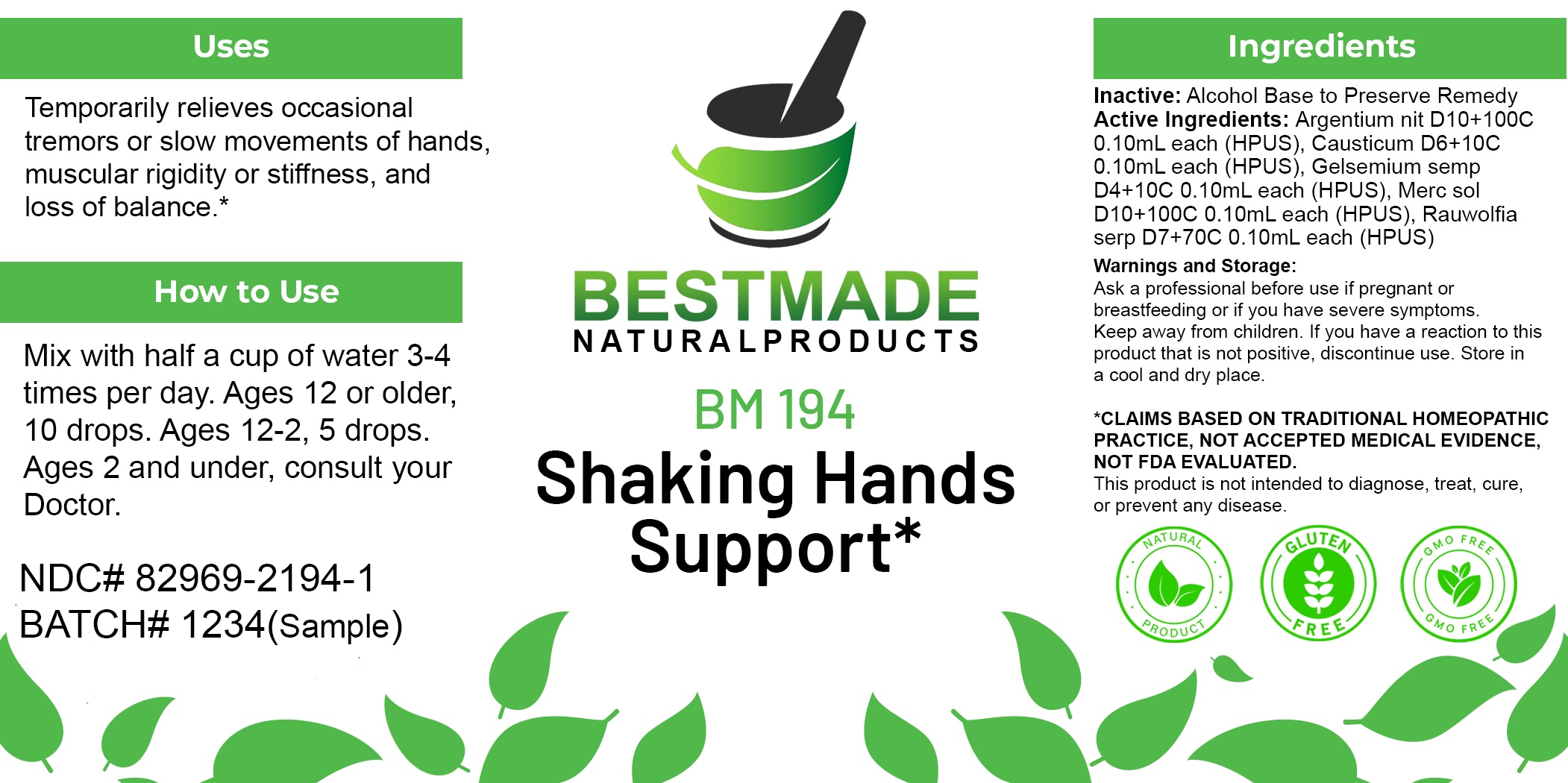 DRUG LABEL: Bestmade Natural Products BM194
NDC: 82969-2194 | Form: LIQUID
Manufacturer: Bestmade Natural Products
Category: homeopathic | Type: HUMAN OTC DRUG LABEL
Date: 20250221

ACTIVE INGREDIENTS: MERCURIUS SOLUBILIS 30 [hp_C]/30 [hp_C]; RAUWOLFIA SERPENTINA 30 [hp_C]/30 [hp_C]; GELSEMIUM SEMPERVIRENS ROOT 30 [hp_C]/30 [hp_C]; SILVER NITRATE 30 [hp_C]/30 [hp_C]; CAUSTICUM 30 [hp_C]/30 [hp_C]
INACTIVE INGREDIENTS: ALCOHOL 30 [hp_C]/30 [hp_C]

BM194

DOSAGE AND ADMINISTRATION

How to Use

Mix with half a cup of water 3-4 times per day. Ages 12 or older, 10 drops. Ages 12-2, 5 drops. Ages 2 and under, consult your Doctor.

Inactive:

Alcohol Base to Preserve Product

ACTIVE INGREDIENTS

Argentium nit D10+100C 0.10mL each (HPUS), Causticum D6+10C 0.10mL each (HPUS), Gelsemium semp D4+10C 0.10mL each (HPUS), Merc sol D10+100C 0.10mL each (HPUS), Rauwolfia serp D7+70C 0.10mL each (HPUS)

KEEP OUT OF REACH OF CHILDREN

Warnings and Storage:

Ask a professional before use if pregnant or breastfeeding or if you have severe symptoms.

Keep away from children. If you have a reaction to this product that is not positive, discontinue use. Store in a cool and dry place

*CLAIMS BASED ON TRADITIONAL HOMEOPATHIC PRACTICE, NOT ACCEPTED MEDICAL EVIDENCE NOT FDA EVALUATED.
This product is not intended to diagnose, treat, cure, or prevent any disease.

Warnings and Storage:

Ask a professional before use if pregnant or breastfeeding or if you have severe symptoms.

Keep away from children. If you have a reaction to this product that is not positive, discontinue use. Store in a cool and dry place

*CLAIMS BASED ON TRADITIONAL HOMEOPATHIC PRACTICE, NOT ACCEPTED MEDICAL EVIDENCE NOT FDA EVALUATED.
This product is not intended to diagnose, treat, cure, or prevent any disease.

Uses
Temporarily relieves occasional tremors or slow movements of hands, muscular rigidity or stiffness, and loss of balance.*

Uses
Temporarily relieves occasional tremors or slow movements of hands, muscular rigidity or stiffness, and loss of balance.*

Entire package label